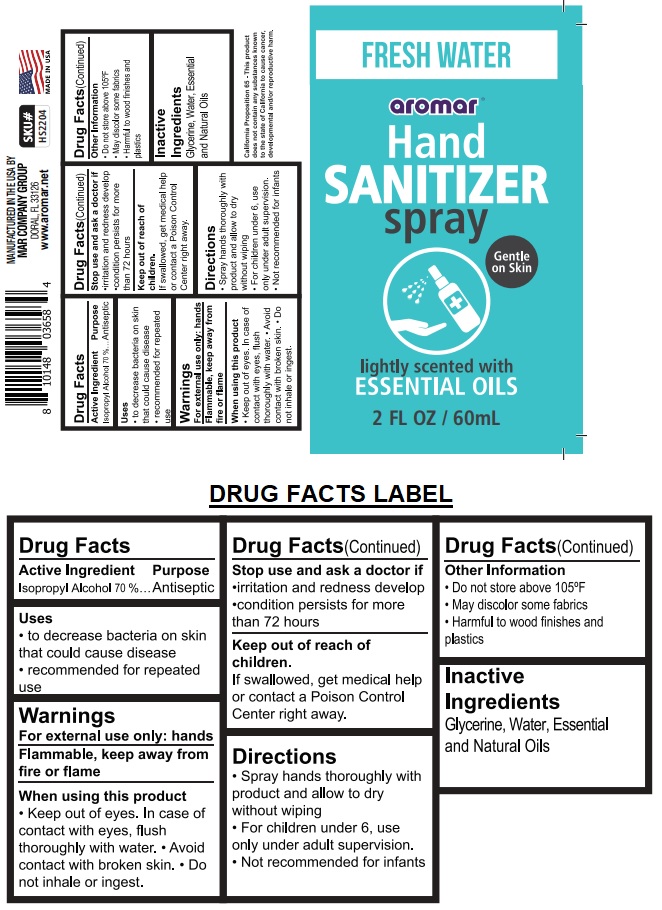 DRUG LABEL: Fresh Water Aromar Hand Sanitizer
NDC: 73717-404 | Form: SPRAY
Manufacturer: Mar Company Distributors, LLC
Category: otc | Type: HUMAN OTC DRUG LABEL
Date: 20200321

ACTIVE INGREDIENTS: ISOPROPYL ALCOHOL 70 mL/100 mL
INACTIVE INGREDIENTS: GLYCERIN; WATER

FRESH WATER aromar HAND SANITIZER Spray

Active Ingredient

Isopropyl Alcohol 70%

Purpose

Antiseptic

Uses

- to decrease bacteria on skin that could cause disease
- recommended for repeated use

Warnings

For external use only: hands

Flammable, keep away from fire and flame

When using this product.

- Keep out of eyes. In case of contact with eyes, flush thoroughly with water.
- Avoid contact with broken skin.
- Do not inhale or ingest.

Stop use and ask a doctor if

- irritation and redness develop
- condition persists for more than 72 hours

Keep out of reach of children.

If swallowed, get medical help or contact a Poison Control Center right away.

Directions

• Spray hands thoroughly with product and allow to dry without wiping
• For children under 6, use only under adult supervision
• Not recommended for infants

Other Information

• Do not store above 105°F
• May discolor some fabrics
• Harmful to wood finishes and plastics

Inactive Ingredients

Glycerine, Water, Essential and Natural Oils

FRESH WATER

aromar™

Gentle on Skin

lightly scented with

ESSENTIAL OILS

MANUFACTURED IN THE USA BY

MAR COMPANY GROUP

DORAL, FL 33126

www.aromar.net

California Proposition 65 - This product does not contain any substances known to the state of California to cause cancer, development and/or reproductive harm.